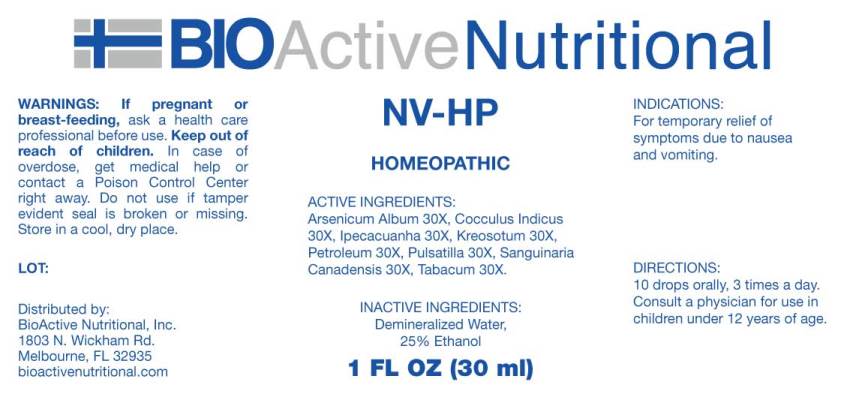 DRUG LABEL: NV-HP
NDC: 43857-0221 | Form: LIQUID
Manufacturer: BioActive Nutritional, Inc.
Category: homeopathic | Type: HUMAN OTC DRUG LABEL
Date: 20181129

ACTIVE INGREDIENTS: ARSENIC TRIOXIDE 30 [hp_X]/1 mL; ANAMIRTA COCCULUS SEED 30 [hp_X]/1 mL; IPECAC 30 [hp_X]/1 mL; WOOD CREOSOTE 30 [hp_X]/1 mL; KEROSENE 30 [hp_X]/1 mL; ANEMONE PULSATILLA 30 [hp_X]/1 mL; SANGUINARIA CANADENSIS ROOT 30 [hp_X]/1 mL; TOBACCO LEAF 30 [hp_X]/1 mL
INACTIVE INGREDIENTS: WATER; ALCOHOL

Drug Facts:

ACTIVE INGREDIENTS:

Arsenicum Album 30X, Cocculus Indicus 30X, Ipecacuanha 30X, Kreosotum 30X, Petroleum 30X, Pulsatilla (Vulgaris) 30X, Sanguinaria Canadensis 30X, Tabacum 30X.

INDICATIONS:

For temporary relief of symptoms due to nausea and vomiting.

WARNINGS:

If pregnant or breast-feeding, ask a health care professional before use.

Keep out of reach of children. In case of overdose, get medical help or contact a Poison Control Center right away.

Do not use if tamper evident seal is broken or missing.

Store in a cool, dry place.

Keep out of reach of children. In case of overdose, get medical help or contact a Poison Control Center right away.

DIRECTIONS:

10 drops orally, 3 times a day. Consult a physician for use in children under 12 years of age.

INDICATIONS:

For temporary relief of symptoms due to nausea and vomiting.

INACTIVE INGREDIENTS:

Demineralized Water, 25% Ethanol

QUESTIONS:

Distributed by:

BioActive Nutritional, Inc.

1803 N. Wickham Rd.

Melbourne, FL 32935

bioactivenutritional.com

PACKAGE DISPLAY LABEL:

BIOActive Homeopathic
NV-HP
HOMEOPATHIC
1 FL OZ (30 ml)